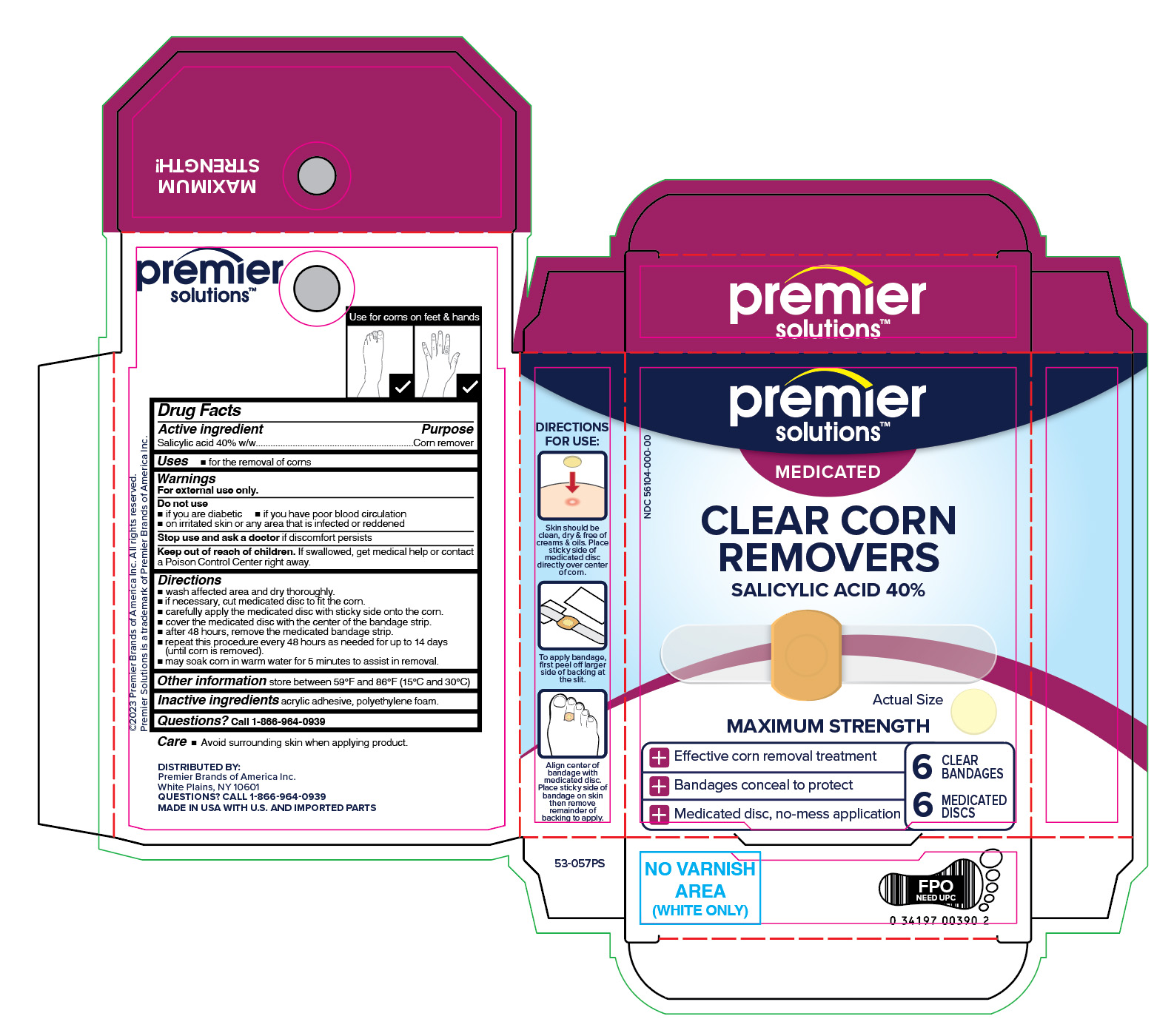 DRUG LABEL: Salicylic Acid
NDC: 56104-258 | Form: PATCH
Manufacturer: Premier Brands of America Inc.
Category: otc | Type: HUMAN OTC DRUG LABEL
Date: 20260115

ACTIVE INGREDIENTS: SALICYLIC ACID 40 mg/12 1
INACTIVE INGREDIENTS: HIGH DENSITY POLYETHYLENE

Premier Solutions Clear Medicated Corn Remover

Active ingredient

Salicylic acid 40% w/w

Purpose

Corn remover

Use

- for the removal of corns

Warnings

For external use only.

Do not use

- if you are a diabetic
- if you have poor blood circulation
- on irritated skin or any area that is infected or reddened

Stop use and ask a doctor if

discomfort persists

Keep out of reach of children.

If swallowed, get medical help or contact a Poison Control Center right away.

Directions

- wash affected area and dry area thoroughly.
- if necessary, cut medicated disc to fit the corn.
- carefully apply the medicated with sticky side onto the corn
- cover the medicated disc with the center of the bandage strip.
- after 48 hours, remove the medicated bandage strip.
- repeat this procedure every 48 hours as needed for up to 14 days (until corn is removed).
- may soak corn in warm water for 5 minutes to assist in removal.

Other information

store between 59° and 86°F (15° and 30°C)

Inactive ingredients

acrylic adhesive, polyethylene foam.

Questions?

Call 1-866-964-0939

Principle Display Panel

Premier Solutions

Medicated Clear

Corn Removers

SALICYLIC ACID 40%

MAXIMUM

STRENGTH

Effective corn removal treatment

Conceals & protects

Medicated disc, no-mess application

6 MEDICATED DISCS | 6 CLEAR STRIPS